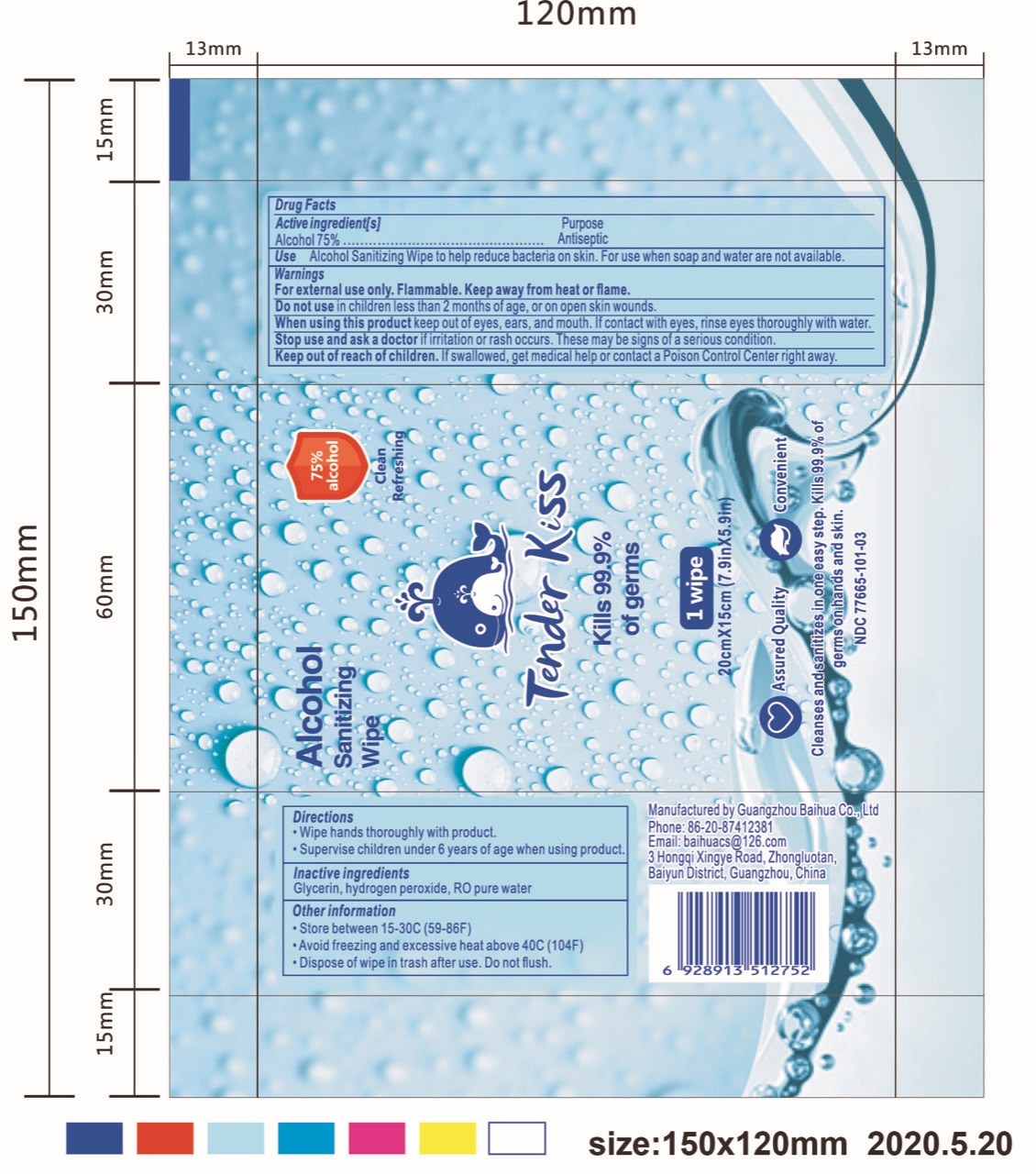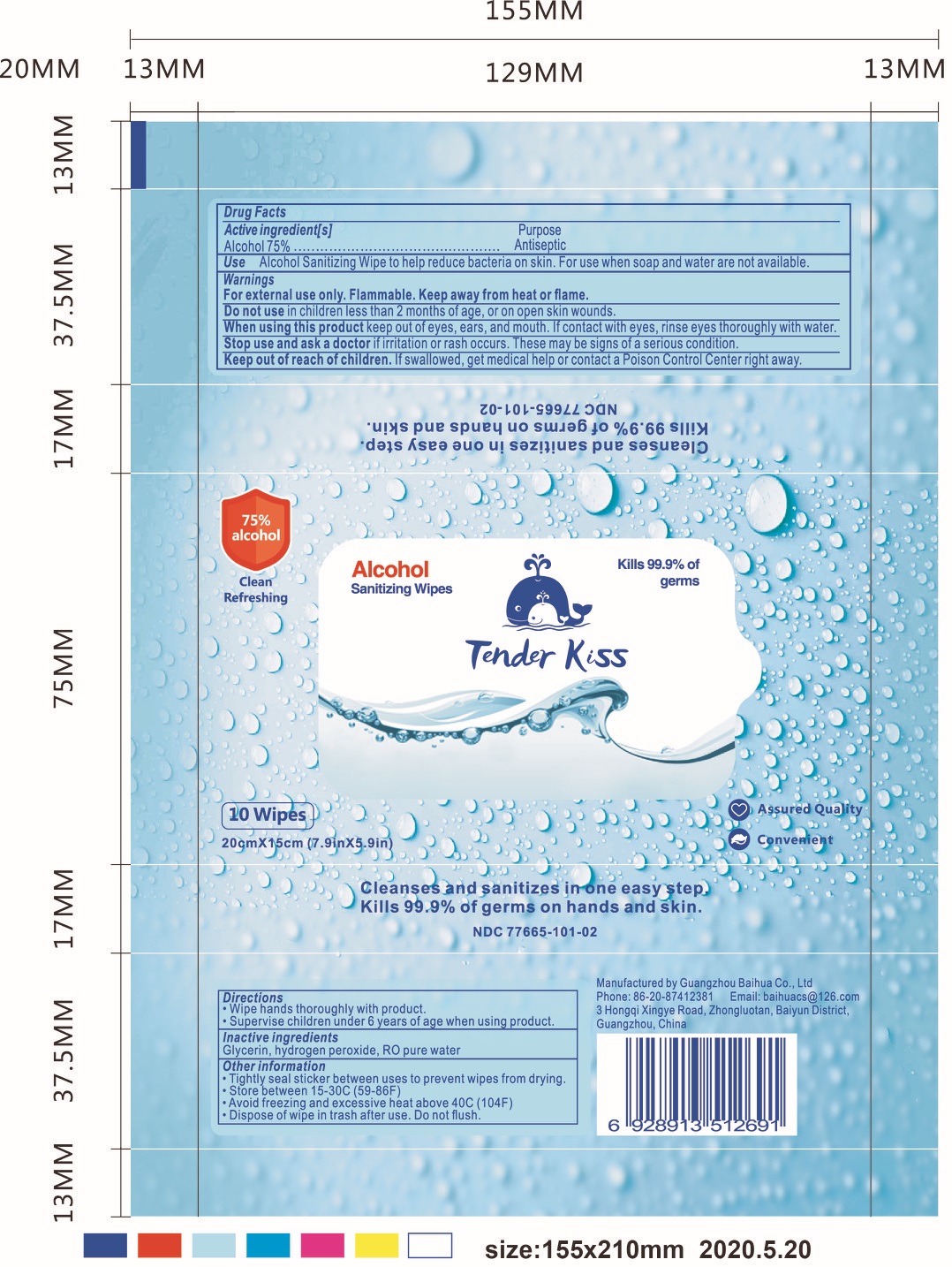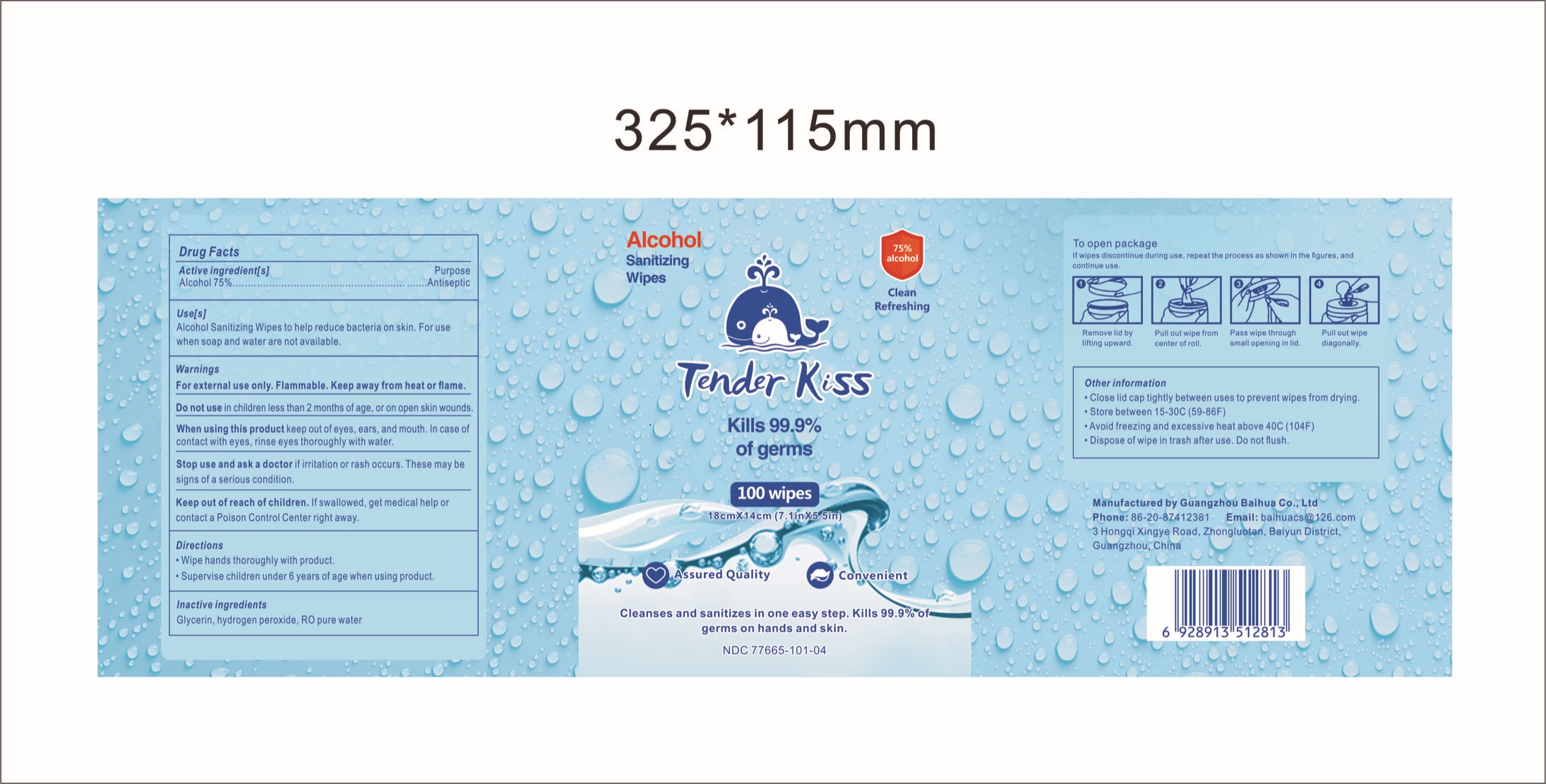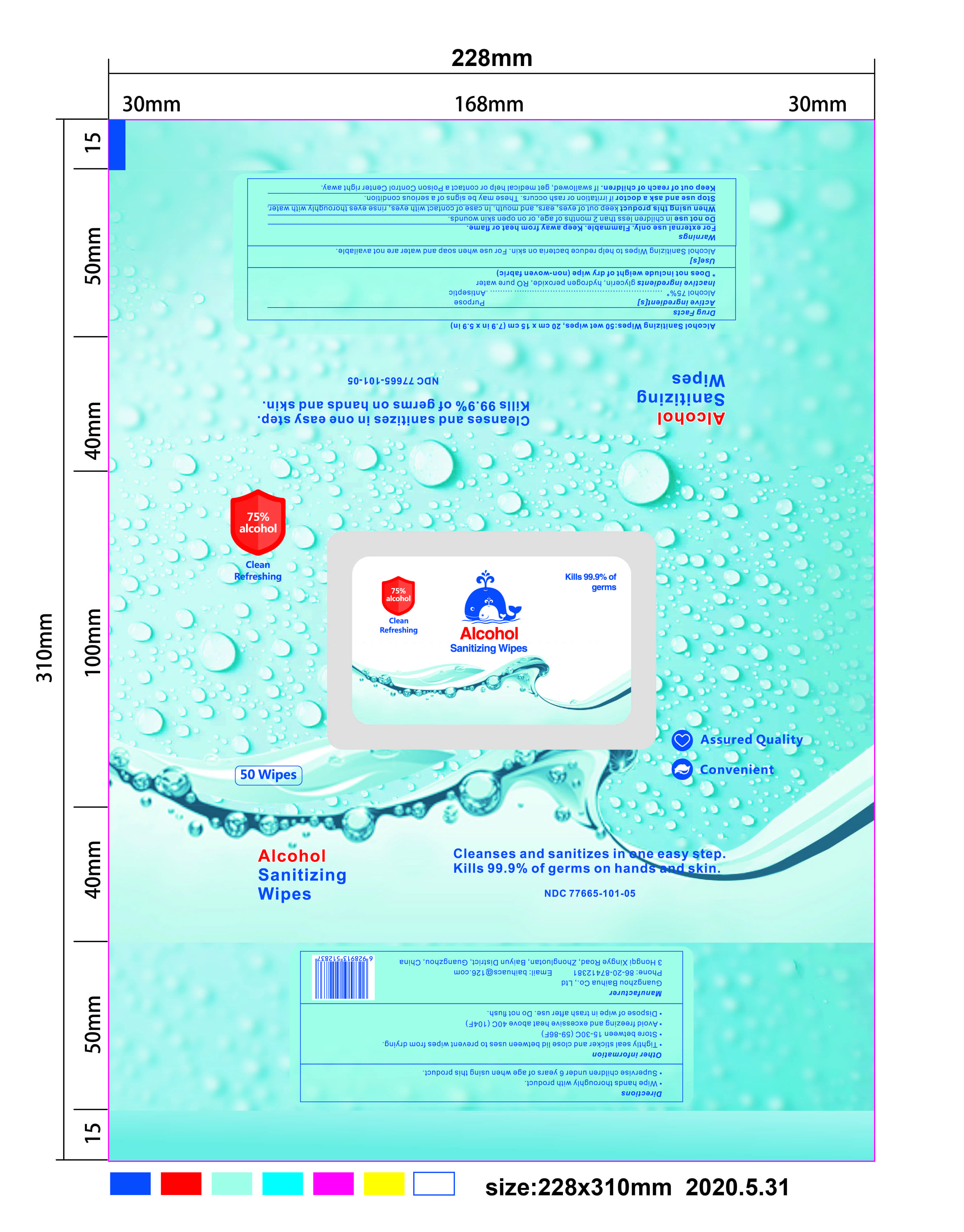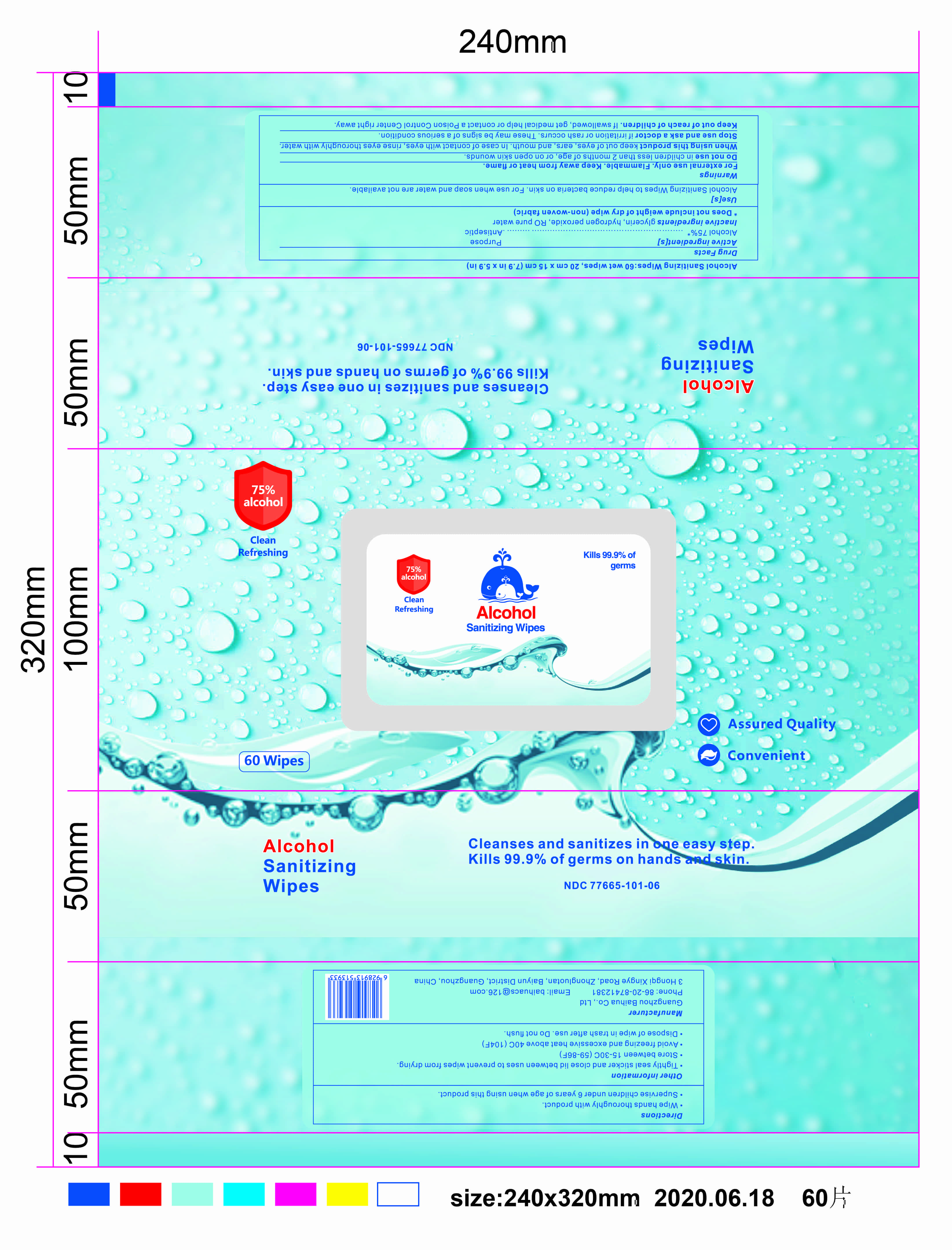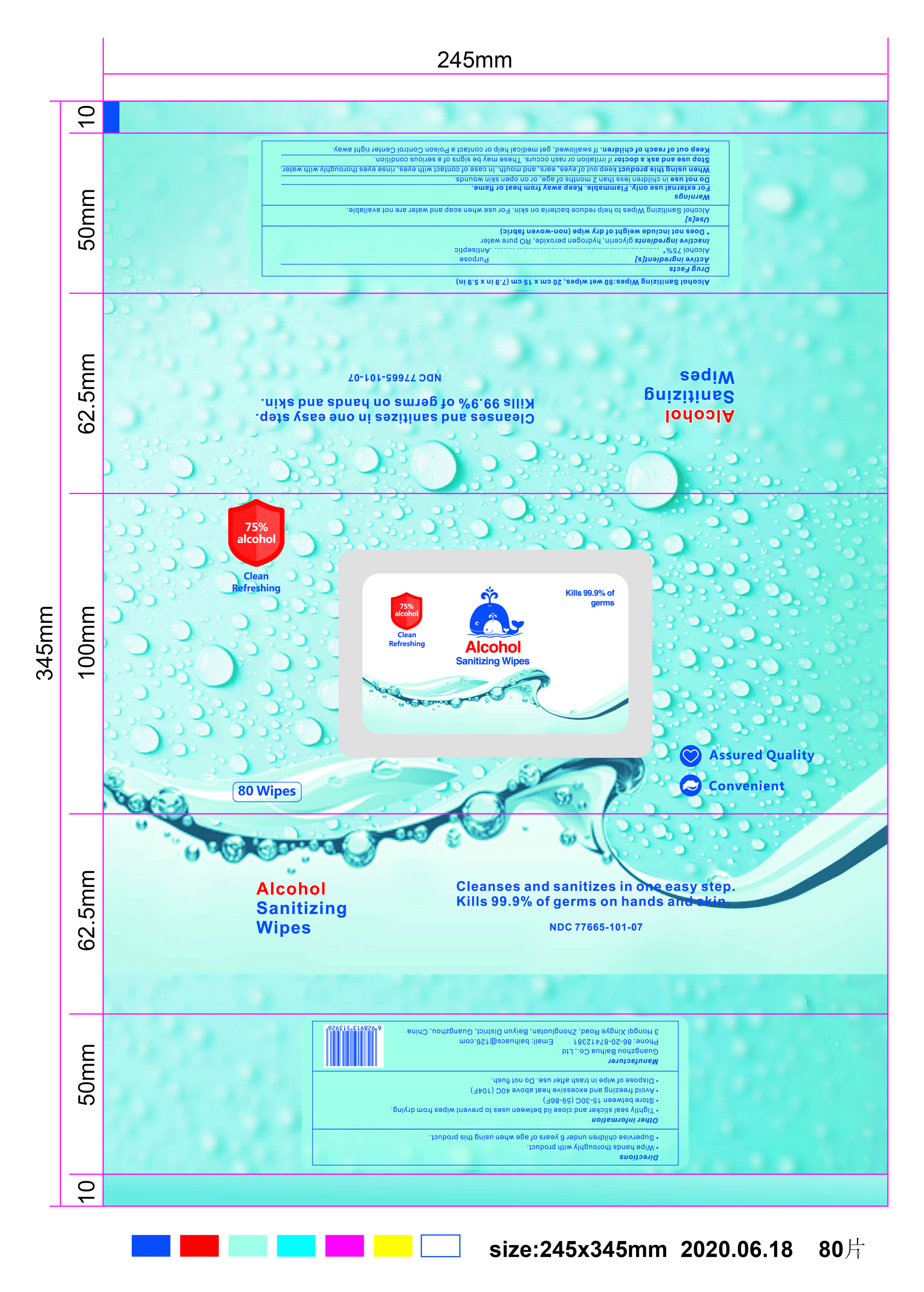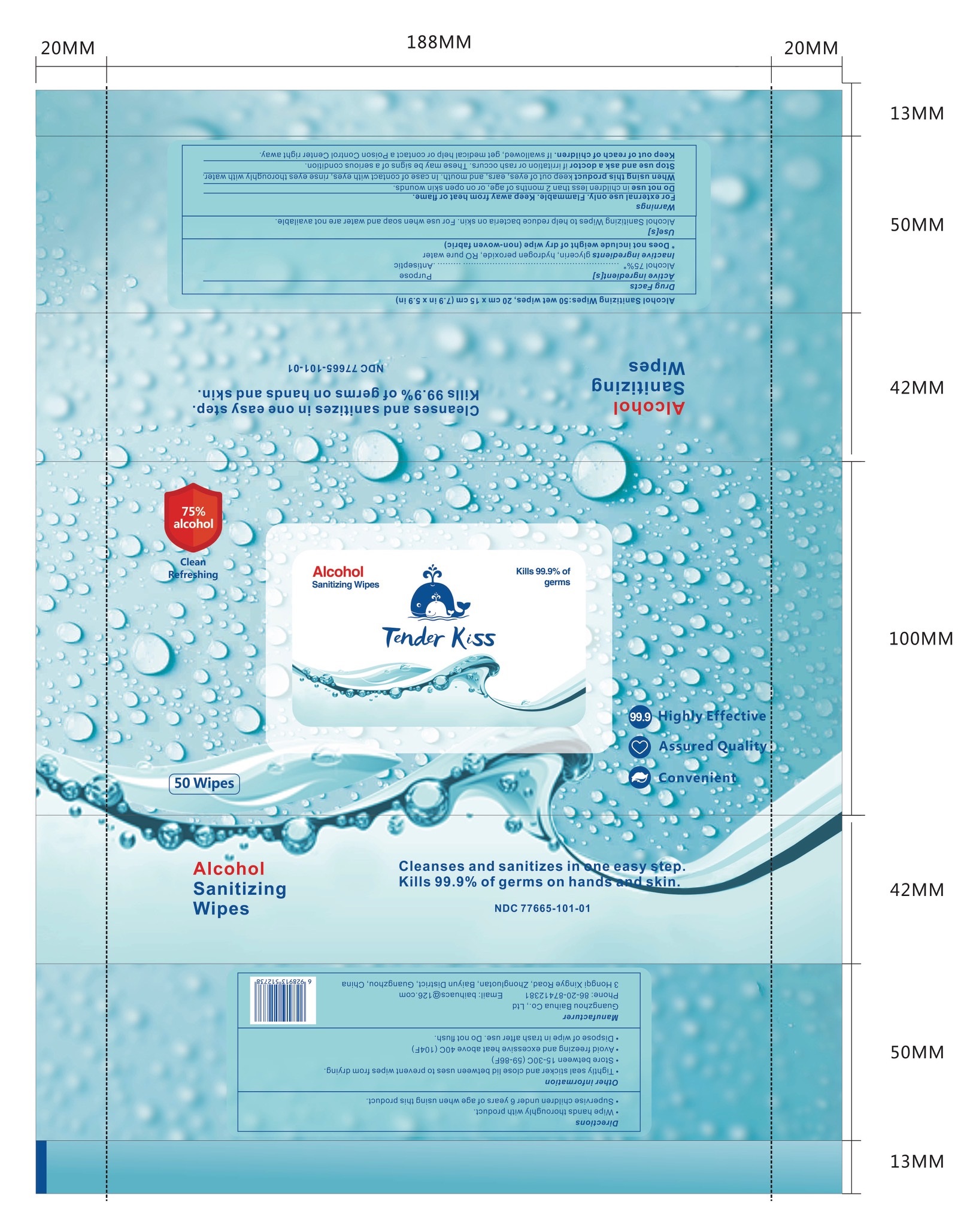 DRUG LABEL: Alcohol Sanitizing Wipes
NDC: 77665-101 | Form: CLOTH
Manufacturer: Guangzhou Baihua Co., Ltd.
Category: otc | Type: HUMAN OTC DRUG LABEL
Date: 20211216

ACTIVE INGREDIENTS: ALCOHOL 75 mL/100 mL
INACTIVE INGREDIENTS: GLYCERIN 1.45 mL/100 mL; HYDROGEN PEROXIDE 0.125 mL/100 mL; WATER

Purpose

Antiseptic, Alcohol Sanitizing Wipes

Active Ingredient(s)

Alcohol 75% v/v. Purpose: Antiseptic

This is a sanitizing wipe manufactured according to the Temporary Policy for Preparation of Certain Alcohol-Based Hand Sanitizer Products During the Public Health Emergency (CoViD-19); Guidance for Industry.

The sanitizing wipe is manufactured using only the following United States Pharmacopoeia (USP) grade ingredients in the preparation of the product (percentage in final product formulation) consistent with World Health Organization (WHO) recommendations:

1. Alcohol (ethanol) (USP or Food Chemical Codex (FCC) grade) (75%, volume/volume (v/v)) in an aqueous solution denatured according to Alcohol and Tobacco Tax and Trade Bureau regulations in 27 CFR part 20.
2. Glycerol (1.45% v/v).
3. Hydrogen peroxide (0.125% v/v).
4. Sterile distilled water or boiled cold water.

The firm does not add other active or inactive ingredients. Different or additional ingredients may impact the quality and potency of the product.

Use

Alcohol Sanitizing Wipes to help reduce bacteria on skin. For use when soap and water are not available.

Warnings

For external use only. Flammable. Keep away from heat or flame

Do not use

- in children less than 2 months of age
- on open skin wounds

When using this product keep out of eyes, ears, and mouth. In case of contact with eyes, rinse eyes thoroughly with water.
Stop use and ask a doctor if irritation or rash occurs. These may be signs of a serious condition.
Keep out of reach of children. If swallowed, get medical help or contact a Poison Control Center right away.

Stop use and ask a doctor if irritation or rash occurs. These may be signs of a serious condition.

Keep out of reach of children. If swallowed, get medical help or contact a Poison Control Center right away.

Directions

- Wipe hands thoroughly with product.
- Supervise children under 6 years of age when using this product.

Other information

- Tightly seal sticker and close lid between uses to prevent wipes from drying.
- Store between 15-30C (59-86F)
- Avoid freezing and excessive heat above 40C (104F)
- Dispose of wipes in trash after use. Do not flush.

Inactive ingredients

glycerin, hydrogen peroxide, RO pure water

Package Label - Principal Display Panel

80 wipes b NDC: 77665-101-07

60 wipes b NDC: 77665-101-06

50 wipes b NDC: 77665-101-05

100 wipes NDC: 77665-101-04

1 wipe NDC: 77665-101-03

10 wipes NDC: 77665-101-02

50 wipes NDC: 77665-101-01